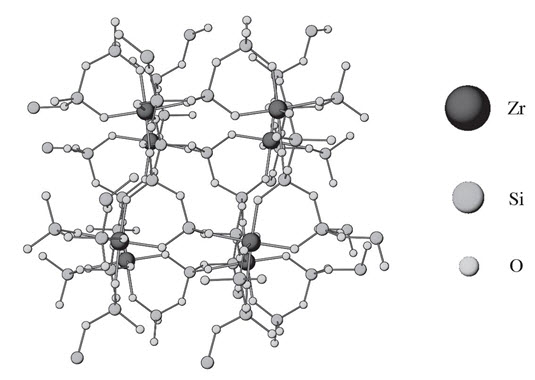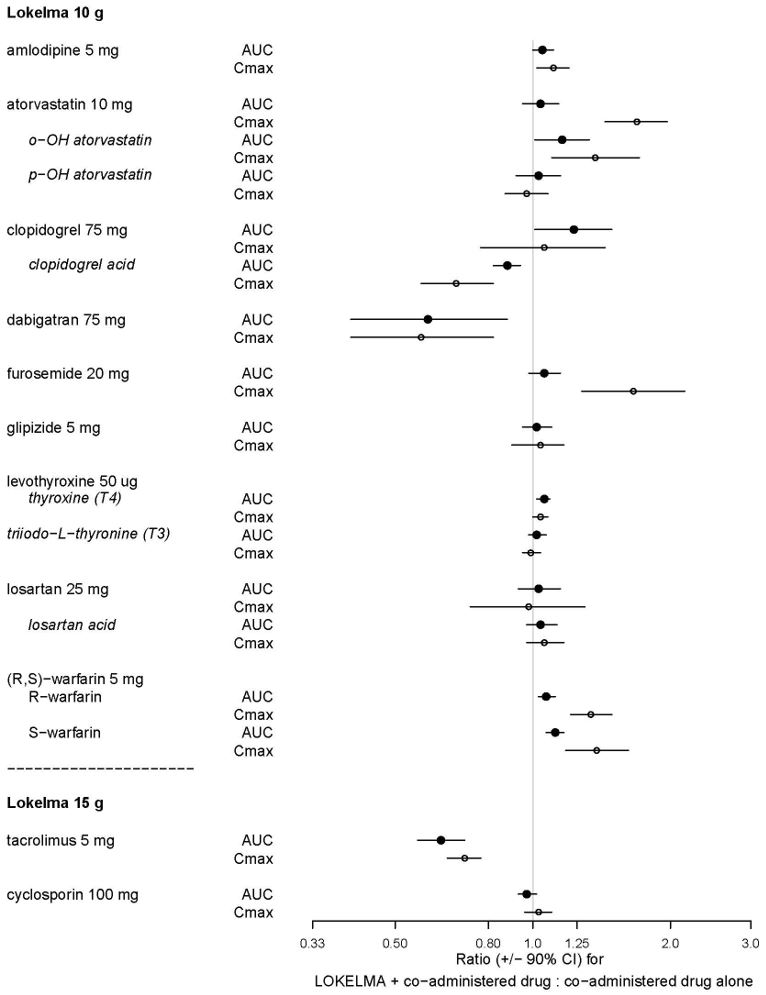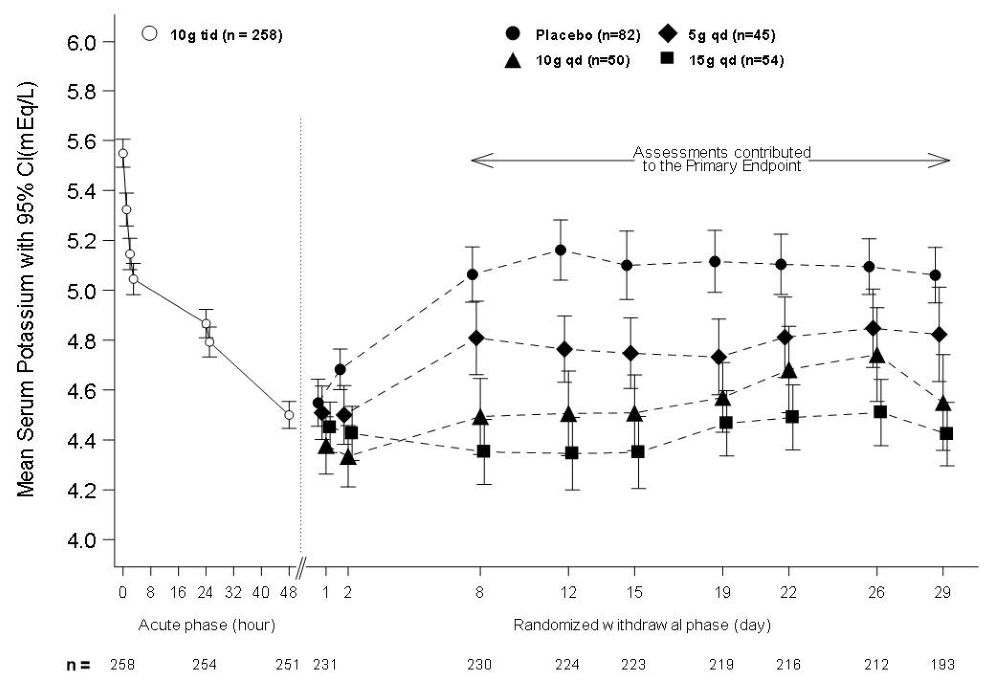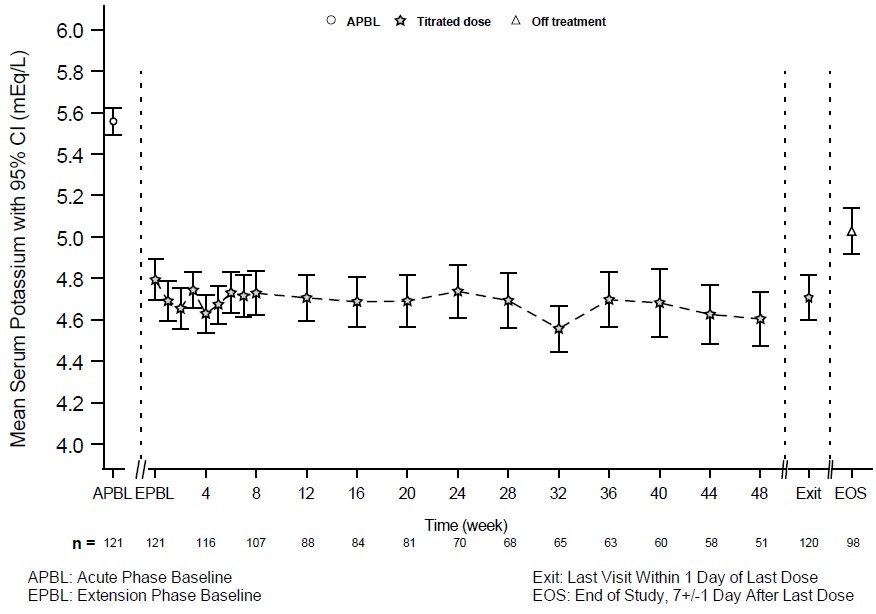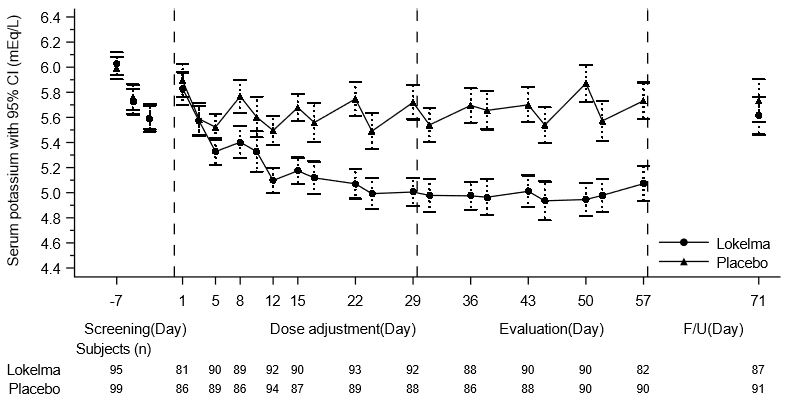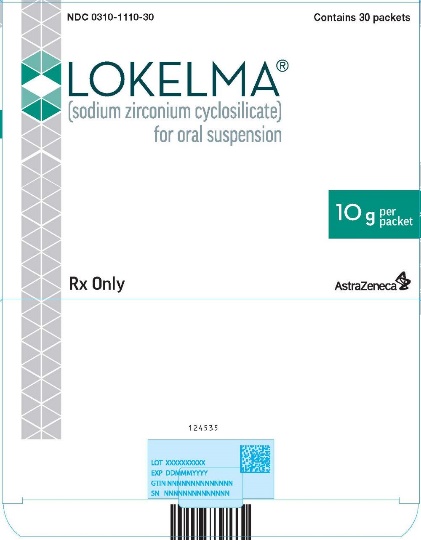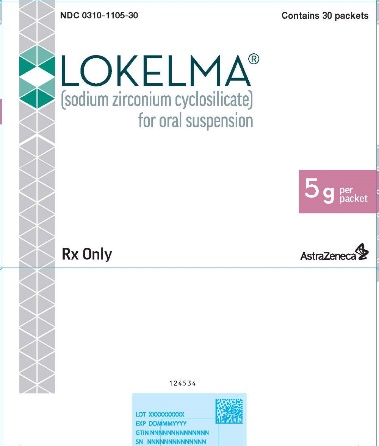 DRUG LABEL: LOKELMA
NDC: 0310-1105 | Form: POWDER, FOR SUSPENSION
Manufacturer: AstraZeneca Pharmaceuticals LP
Category: prescription | Type: HUMAN PRESCRIPTION DRUG LABEL
Date: 20240208

ACTIVE INGREDIENTS: SODIUM ZIRCONIUM CYCLOSILICATE 5 g/5 g

HIGHLIGHTS OF PRESCRIBING INFORMATION

These highlights do not include all the information needed to use LOKELMA® safely and effectively. See full prescribing information for LOKELMA®.
LOKELMA® (sodium zirconium cyclosilicate) for oral suspension
Initial U.S. Approval: 2018

1 INDICATIONS AND USAGE

LOKELMA is a potassium binder indicated for the treatment of hyperkalemia in adults. (1)

Limitation of Use

LOKELMA should not be used as an emergency treatment for life-threatening hyperkalemia because of its delayed onset of action. (1)

2 DOSAGE AND ADMINISTRATION

- Recommended starting dose is 10 g administered three times a day for up to 48 hours. (2.1)
- For maintenance treatment, recommended dose is 10 g once daily. Adjust dose at one-week intervals as needed (by 5 g daily) to obtain desired serum potassium target range. (2.1)

Patients on Chronic Hemodialysis

- Recommended starting dose is 5 g once daily on non-dialysis days. (2.2)

See full Prescribing Information for additional dosing instructions, as well as reconstitution and administration instructions for the oral suspension.

3 DOSAGE FORMS AND STRENGTHS

- For oral suspension: 5 g per packet (3)
- For oral suspension: 10 g per packet (3)

4 CONTRAINDICATIONS

None. (4)

5 WARNINGS AND PRECAUTIONS

- Gastrointestinal Adverse Events in Patients with Motility Disorders. (5.1)
- Edema. (5.2)
- Hypokalemia in patients on hemodialysis. (5.3)
- LOKELMA has radio-opaque properties and, therefore, may give the appearance typical of an imaging agent during abdominal X-ray procedures. (5.4)

6 ADVERSE REACTIONS

Most common adverse reactions with LOKELMA: mild to moderate edema. (6.1)

To report SUSPECTED ADVERSE REACTIONS, contact AstraZeneca at 1-800-236-9933 or FDA at 1-800-FDA-1088 or www.fda.gov/medwatch.

7 DRUG INTERACTIONS

In general, other oral medications should be administered at least 2 hours before or 2 hours after LOKELMA. (2.3, 7, 12.3)

FULL PRESCRIBING INFORMATION

1 INDICATIONS AND USAGE

LOKELMA is indicated for the treatment of hyperkalemia in adults.

Limitation of Use

LOKELMA should not be used as an emergency treatment for life-threatening hyperkalemia because of its delayed onset of action [see Clinical Pharmacology (12.2) and Clinical Studies (14)].

2 DOSAGE AND ADMINISTRATION

2.1 Recommended Dosage

For initial treatment of hyperkalemia, the recommended dose of LOKELMA is 10 g administered three times a day for up to 48 hours. Administer LOKELMA orally as a suspension in water [see Dosage and Administration (2.3)].

For continued treatment, the recommended dose is 10 g once daily. Monitor serum potassium and adjust the dose of LOKELMA based on the serum potassium level and desired target range. During maintenance treatment, up-titrate based on the serum potassium level at intervals of 1-week or longer and in increments of 5 g. Decrease the dose of LOKELMA or discontinue if the serum potassium is below the desired target range. The recommended maintenance dose range is from 5 g every other day to 15 g daily.

2.2 Dosage Adjustment for Patients on Chronic Hemodialysis

For patients on chronic hemodialysis, administer LOKELMA only on non-dialysis days.

The recommended starting dose is 5 g once daily on non-dialysis days. Consider a starting dose of 10 g once daily on non-dialysis days in patients with serum potassium greater than 6.5 mEq/L. Monitor serum potassium and adjust the dose of LOKELMA based on the pre-dialysis serum potassium value after the long inter-dialytic interval and desired target range.

During initiation and after a dose adjustment, assess serum potassium after one week. The recommended maintenance dose range is from 5 g to 15 g once daily, on non-dialysis days.

Discontinue or decrease the dose of LOKELMA if:

- serum potassium falls below the desired target range based on the pre-dialysis value after the long interdialytic interval, or;
- the patient develops clinically significant hypokalemia

2.3 Reconstitution and Administration

In general, other oral medications should be administered at least 2 hours before or 2 hours after LOKELMA [see Drug Interactions (7)].

Instruct patients to empty the entire contents of the packet(s) into a drinking glass containing approximately 3 tablespoons of water or more if desired. Stir well and drink immediately. If powder remains in the drinking glass, add water, stir and drink immediately. Repeat until no powder remains to ensure the entire dose is taken.

3 DOSAGE FORMS AND STRENGTHS

For oral suspension: 5 g or 10 g of white to grey powder in a foil-lined packet.

4 CONTRAINDICATIONS

None.

5 WARNINGS AND PRECAUTIONS

5.1 Gastrointestinal Adverse Events in Patients with Motility Disorders

Avoid use of LOKELMA in patients with severe constipation, bowel obstruction or impaction, including abnormal post-operative bowel motility disorders, because LOKELMA has not been studied in patients with these conditions and may be ineffective and may worsen gastrointestinal conditions.

5.2 Edema

Each 5 g dose of LOKELMA contains approximately 400 mg of sodium, but the extent of absorption by the patient is unknown. In clinical trials of LOKELMA in patients who were not on dialysis, edema was observed and was generally mild to moderate in severity and was more commonly seen in patients treated with 15 g once daily. Monitor for signs of edema, particularly in patients who should restrict their sodium intake or are prone to fluid overload (e.g., heart failure or renal disease). Advise patients to adjust dietary sodium, if appropriate. Increase the dose of diuretics as needed [see Adverse Reactions (6)].

In a clinical trial of LOKELMA in patients on chronic hemodialysis in which most patients were treated with doses of 5 to 10 g once daily on non-dialysis days, there was no difference in the mean change from baseline in interdialytic weight gain (a measure of fluid retention) between the LOKELMA and placebo groups.

5.3 Hypokalemia in Patients on Hemodialysis

Patients on hemodialysis may be prone to acute illness that can increase the risk of hypokalemia on LOKELMA (e.g., illnesses associated with decreased oral intake, diarrhea). Consider adjusting Lokelma dose based on potassium levels in these settings.

5.4 Diagnostic Tests

LOKELMA has radio-opaque properties and, therefore, may give the appearance typical of an imaging agent during abdominal X-ray procedures.

6 ADVERSE REACTIONS

The following adverse reactions are discussed in greater detail elsewhere in the label:

- Edema [see Warnings and Precautions (5.2)].

6.1 Clinical Studies Experience

Because clinical studies are conducted under widely varying conditions, adverse reaction rates observed in the clinical studies of a drug cannot be directly compared to rates in the clinical studies of another drug and may not reflect the rates observed in practice.

The total exposure to LOKELMA in the safety and efficacy clinical trials of patients not on dialysis with hyperkalemia was 1,760 patients with 652 patients exposed to LOKELMA for at least 6 months and 507 patients exposed for at least one year.

The population (n=1,009) in the placebo-controlled trials included patients aged 22 to 96 years, females (n=454), Caucasians (n=859) and Blacks (n=130). Patients had hyperkalemia in association with comorbid diseases such as chronic kidney disease, heart failure, and diabetes mellitus.

In placebo-controlled trials in which patients who were not on dialysis were treated with once daily doses of LOKELMA for up to 28 days, edema was reported in 4.4% of patients receiving 5 g, 5.9% of patients receiving 10 g and 16.1% of patients receiving 15 g LOKELMA compared to 2.4% of patients receiving placebo. In longer-term uncontrolled trials in which most patients were maintained on doses <15 g once daily, adverse reactions of edema (edema, generalized edema and peripheral edema) were reported in 8% to 11% of patients.

In a pooled analysis of clinical studies conducted in countries with a predominantly Asian population, constipation occurred in patients receiving LOKELMA with an estimated incidence of 9% and 5% for the 10 g and 5 g dose respectively. Constipation was resolved with dose adjustment or treatment discontinuation. No cases of constipation were reported in patients receiving placebo.

Laboratory Abnormalities

In clinical trials in patients who were not on dialysis, 4.1% of LOKELMA-treated patients developed hypokalemia with a serum potassium value less than 3.5 mEq/L, which resolved with dosage reduction or discontinuation of LOKELMA. In a clinical trial of LOKELMA in patients on chronic hemodialysis, 5% of patients developed pre-dialysis hypokalemia (serum potassium <3.5 mEq/L) in both the LOKELMA and placebo groups; 3% and 1% of patients developed a serum potassium < 3.0 mEq/L in the LOKELMA and placebo groups, respectively.

7 DRUG INTERACTIONS

LOKELMA can transiently increase gastric pH. As a result, LOKELMA can change the absorption of co-administered drugs that exhibit pH-dependent solubility, potentially leading to altered efficacy or safety of these drugs when taken close to the time LOKELMA is administered. In general, other oral medications should be administered at least 2 hours before or 2 hours after LOKELMA [see Dosage and Administration (2.3) and Clinical Pharmacology (12.3)]. LOKELMA is not expected to impact systemic exposure of drugs that do not exhibit pH-dependent solubility and so spacing is not needed if it has been determined that the concomitant medication does not exhibit pH-dependent solubility.

8 USE IN SPECIFIC POPULATIONS

8.1 Pregnancy

Risk Summary

LOKELMA is not absorbed systemically following oral administration and maternal use is not expected to result in fetal exposure to the drug.

8.2 Lactation

Risk Summary

LOKELMA is not absorbed systemically following oral administration, and breastfeeding is not expected to result in exposure of the child to LOKELMA.

8.4 Pediatric Use

Safety and effectiveness in pediatric patients have not been established.

8.5 Geriatric Use

Of the total number of subjects in clinical studies of LOKELMA, 58% were age 65 and over, while 25% were 75 and over. No overall differences in safety or effectiveness were observed between these patients and younger patients.

11 DESCRIPTION

LOKELMA is a powder for oral suspension. The active ingredient in LOKELMA is sodium zirconium cyclosilicate, a potassium binder. Sodium zirconium cyclosilicate is a non-absorbed zirconium silicate that preferentially exchanges potassium for hydrogen and sodium. LOKELMA is an odorless, insoluble white to grey powder for oral suspension. It has a mean particle size of 20 µm and includes no more than 3% of particles with a diameter below 3 µm. Each 5 g of sodium zirconium cyclosilicate contains 400 mg of sodium.

The chemical formula of sodium zirconium cyclosilicate is Na~1.5H~0.5ZrSi3O9•2–3H2O.

Figure 1: Crystal Structure of Sodium Zirconium Cyclosilicate

12 CLINICAL PHARMACOLOGY

12.1 Mechanism of Action

LOKELMA (sodium zirconium cyclosilicate) is a non-absorbed zirconium silicate that preferentially captures potassium in exchange for hydrogen and sodium. In vitro, LOKELMA has a high affinity for potassium ions, even in the presence of other cations such as calcium and magnesium. LOKELMA increases fecal potassium excretion through binding of potassium in the lumen of the gastrointestinal tract. Binding of potassium reduces the concentration of free potassium in the gastrointestinal lumen, thereby lowering serum potassium levels.

12.2 Pharmacodynamics

In a study in healthy adult subjects, LOKELMA administered as 5 g or 10 g once daily for four days caused a dose-dependent increase in fecal potassium excretion. Corresponding dose-dependent decreases in urinary potassium excretion and serum potassium were also observed.

In patients with hyperkalemia treated with LOKELMA 10 g three times a day for up to 48 hours, reductions in serum potassium were observed one hour after initiation of therapy; serum potassium concentrations continued to decline over the 48-hour treatment period [see Clinical Studies (14.2)]. In patients not continuing LOKELMA, potassium levels increased. Patients with higher starting serum potassium levels or receiving a higher dose have greater reductions in serum potassium.

LOKELMA causes a small dose-dependent increase in serum bicarbonate concentrations (1.1 mmol/L at 5 g once daily, 2.3 mmol/L at 10 g once daily and 2.6 mmol/L at 15 g once daily as compared with a mean increase of 0.6 mmol/L in patients treated with placebo). The clinical significance of this finding is unclear.

12.3 Pharmacokinetics

LOKELMA is an inorganic, insoluble compound that is not subject to enzymatic metabolism. In a clinical study in patients with hyperkalemia in which zirconium concentrations were measured in the urine and blood, zirconium concentrations were similar in treated and untreated patients (i.e., either undetectable or around the lower limit of quantification of the assay). An in vivo mass balance study in rats showed that LOKELMA was recovered in the feces with no evidence of systemic absorption.

Drug Interactions

Thirty-six (36) drugs were tested in-vitro to determine potential interactions with LOKELMA. Sixteen (16) drugs tested did not show an in vitro interaction with LOKELMA (allopurinol, apixaban, aspirin, captopril, cyclosporine, digoxin, ethinyl estradiol, lisinopril, magnesium, metformin, phenytoin, prednisone, propranolol, quinapril, spironolactone and ticagrelor).

Nine (9) of the 20 drugs that showed an in vitro interaction were subsequently tested in vivo with LOKELMA 10 g in healthy volunteers. Losartan, glipizide and levothyroxine did not show any changes in exposure when co-administered with LOKELMA. However, there was an increase in systemic exposure to weak acids such as furosemide and atorvastatin, and a decrease in systemic exposure to weak bases such as dabigatran when co-administered with LOKELMA, as shown in Figure 2. These changes are consistent with the hypothesis that LOKELMA, by elevating gastric pH, affects the systemic exposure of co-administered drugs whose solubility is pH-dependent [see Drug Interactions (7)].

In another drug-drug interaction study in healthy volunteers, co-administration of LOKELMA 15 g

decreased the systemic exposures of tacrolimus (Figure 2), likely due to LOKELMA’s action on elevating

gastric pH. In the same study, co-administration of LOKELMA and cyclosporine did not show a

clinically meaningful interaction.

Figure 2: Effects of LOKELMA 10 g or 15 g on the Pharmacokinetic Exposures of Other Orally Administered Medications

13 NONCLINICAL TOXICOLOGY

13.1 Carcinogenesis, Mutagenesis, Impairment of Fertility

The following tests for mutagenic potential of sodium zirconium cyclosilicate were negative: (1) the Ames (S. typhimurium and E. coli) test; (2) chromosomal aberration assay in Chinese Hamster Ovary (CHO) cells; and (3) in vivo rat micronucleus assay. Given that zirconium cyclosilicate is not genotoxic, not absorbed from the gastrointestinal tract, and did not cause local gastrointestinal alterations in a chronic toxicity study in dogs, carcinogenicity studies in animals to evaluate tumorigenic potential of sodium zirconium cyclosilicate were not deemed to be necessary.

Fertility in male and female rats has been assessed at doses up to a Human Equivalent Dose (HED) of 58 g per day (the maximum feasible dose) with no adverse effects.

14 CLINICAL STUDIES

14.1 Study 1

The effectiveness of LOKELMA in lowering serum potassium was demonstrated in a two-part, double-blind, randomized, placebo-controlled clinical trial (NCT01737697) in patients with hyperkalemia (5 to 6.5 mEq/L, mean potassium 5.3 mEq/L), Study 1.

In the first phase of the trial (the acute phase), 753 patients were randomized to receive one of four doses of LOKELMA (1.25, 2.5, 5 or 10 g) or placebo, administered three times daily for the initial 48 hours with meals.

The mean age of patients was 66 years, 59% of patients were men, and 86% were Caucasian. Approximately 60% of patients had chronic kidney disease, 10% had heart failure, 62% had diabetes mellitus and 67% were on renin angiotensin aldosterone system (RAAS) inhibitor therapy at baseline.

The primary endpoint in the acute phase was the difference in the exponential rate of change in serum potassium levels during the initial 48 hours of study drug treatment, comparing placebo-treated patients and LOKELMA-treated patients. The study met its primary endpoint demonstrating a greater reduction in serum potassium levels for the 2.5, 5 and 10 g (three times a day) dose groups compared to the placebo group (p<0.001). As displayed in Table 1 for the secondary endpoint of potassium change from baseline, LOKELMA showed dose-dependent reductions in serum potassium at 2.5, 5 and 10 g. In patients administered 10 g TID, the mean serum potassium reduction was -0.7 mEq/L at 48 hours. Patients with higher starting potassium levels had a greater response to LOKELMA. LOKELMA was effective in lowering potassium levels in patients with chronic kidney disease, heart failure, diabetes mellitus and those taking RAAS inhibitor therapy.

Table 1: Study 1 - Potassium Change from Baseline to 48 hours
Mean Serum Potassium Change mEq/L (95% Confidence Intervals) Sample Size | Placebo | 1.25 g TID | 2.5 g TID | 5 g TID | 10 g TID
All Patients | -0.2 (-0.3, -0.2) n=158 | -0.3 (-0.4, -0.2) n=150 | -0.5 (-0.5, -0.4) n=137 | -0.5 (-0.6, -0.5) n=152 | -0.7 (-0.8, -0.7) n=140
Baseline Serum Potassium >5.5 mEq/L | -0.4 (-0.6, -0.3) n=40 | -0.3 (-0.5, -0.2) n=40 | -0.6 (-0.7, -0.4) n=37 | -0.9 (-1.0, -0.7) n=29 | -1.1 (-1.3, -0.9) n=22

Patients who achieved a potassium level between 3.5 and 5 mEq/L after receiving LOKELMA during the acute phase were re-randomized to receive once daily placebo or 1.25, 2.5, 5 or 10 g of once daily LOKELMA for 12 days together with breakfast.

The primary endpoint in the maintenance phase was the difference in the exponential rate of change in serum potassium levels over the 12-day treatment interval, comparing patients receiving LOKELMA and patients receiving placebo. The study met the primary efficacy endpoint at the 5 and 10 g doses when compared with their respective placebo groups (p<0.01 and p<0.001).

14.2 Study 2

The efficacy of LOKELMA was also demonstrated in a two-part trial with an open-label acute phase and a month-long randomized, double-blind, placebo-controlled withdrawal phase (Study 2; NCT02088073).

In the open-label acute phase of Study 2, 258 patients with hyperkalemia (baseline mean 5.6 mEq/L, range 5.1 to 7.4 mEq/L) received 10 g of LOKELMA administered three times daily with meals for 48 hours. As shown in Figure 3, left, average serum potassium levels decreased from 5.6 to 4.5 mEq/L during treatment with LOKELMA in the acute phase.

Following the acute phase of the study, there was a double-blind randomized withdrawal phase where patients who achieved potassium levels between 3.5 and 5 mEq/L were randomized to one of three doses of LOKELMA administered once-daily for 28 days, or placebo just before breakfast. Of the patients enrolled in the acute phase, 92% achieved a potassium level within this range and were enrolled into the second phase of the trial.

The primary endpoint in the randomized withdrawal phase was the mean serum potassium value over the period from Day 8 to Day 29, comparing LOKELMA-treated and placebo-treated patients. All three doses (5, 10 and 15 g) of once daily LOKELMA maintained mean potassium at lower levels than placebo (mean serum potassium was 4.8, 4.5, and 4.4 mEq/L for the 5, 10 and 15 g dose groups, respectively, vs. 5.1 mEq/L in the placebo group, p≤0.001 for all doses, Figure 3, right). A greater proportion of patients had mean serum potassium levels in the normal range (3.5 to 5 mEq/L) while on LOKELMA than while on placebo (80%, 90% and 94% at the 5, 10 and 15 g doses, respectively, vs. 46% on placebo).

Figure 3: Study 2 - Mean Serum Potassium Levels in the Acute and Randomized Withdrawal Phases

Intent-to-Treat population includes subjects with at least one valid serum potassium measurement on or after Day 8

14.3 Eleven-Month Extension Study

Patients who completed the 28-day randomized withdrawal phase had the option to continue treatment with LOKELMA, taken just before breakfast, in an open-label extension phase for up to 11 months (n=123; NCT02107092). Figure 4 shows that the treatment effect on serum potassium was maintained during continued therapy.

Figure 4: 11-Month Open-Label Extension Phase of Study 2 - Mean Serum Potassium (mEq/L)

14.4 Study 3

LOKELMA was evaluated in an open-label 12-month study in 751 hyperkalemic patients (NCT02163499). The mean baseline potassium level in this study was 5.6 mEq/L. Following the acute phase treatment of LOKELMA 10 g three times a day, patients who achieved normokalemia (3.5-5.0 mEq/L) within 72 hours (n=746; 99%) entered the maintenance phase. For maintenance treatment, the initial dosage of LOKELMA was 5 g once daily and was adjusted to a minimum of 5 g every other day up to maximum of 15 g once daily, based on serum potassium level. The treatment effect on serum potassium was maintained during continued therapy.

14.5 Study 4

The effectiveness of LOKELMA in lowering serum potassium was studied in a double-blind, placebo-controlled trial of 196 chronic hemodialysis patients (mean age 58 years, range 20 to 86 years) with persistent pre-dialysis hyperkalemia (mean baseline potassium 5.8 mEq/L) who were randomized to receive LOKELMA 5 g or placebo once daily on non-dialysis days (NCT03303521). During the dose adjustment period (initial 4 weeks), the dose was adjusted weekly in 5 g increments up to 15 g once daily based on pre-dialysis serum potassium measurement after the long inter-dialytic interval to achieve a pre-dialysis serum potassium level between 4.0-5.0 mEq/L. The dose reached at the end of the dose-adjustment period was maintained throughout the subsequent 4-week evaluation period.

The primary endpoint in the trial was the proportion of responders, defined as patients who maintained a pre-dialysis serum potassium between 4.0 and 5.0 mEq/L on at least 3 out of 4 dialysis treatments after the long inter-dialytic interval and who did not receive rescue therapy during the evaluation period. A greater proportion of patients were responders in the LOKELMA arm as compared to placebo (41% vs 1%, respectively; p<0.001). The treatment effect on mean pre-dialysis serum potassium levels was maintained during continued treatment. Mean pre-dialysis serum potassium levels during the study are presented in Figure 5.

Figure 5: Mean Pre-Dialysis Serum Potassium Levels Over Time in Patients on Chronic Hemodialysis

F/U - follow-up period

The displayed error bars correspond to 95% confidence intervals.

n = Number of patients with non-missing potassium measurements at a particular visit.

16 HOW SUPPLIED/STORAGE AND HANDLING

LOKELMA (sodium zirconium cyclosilicate) for oral suspension is supplied as a white to grey powder in foil-lined packets as follows:

LOKELMA (grams) | Single Packet | Box of 11 Packets | Box of 30 Packets
5 | NDC 0310-1105-01 | NDC 0310-1105-39 | NDC 0310-1105-30
10 | NDC 0310-1110-01 | NDC 0310-1110-39 | NDC 0310-1110-30

Storage and Handling

Store LOKELMA at 15°C-30°C (59°F-86°F).

17 PATIENT COUNSELING INFORMATION

Dosing

Instruct the patient how to reconstitute LOKELMA for administration. Inform the patient that it is necessary to drink the full dose [see Dosage and Administration (2.3)].

Instruct dialysis patients who experience acute illness (e.g., decreased oral intake of food or fluids, diarrhea) to contact the health care provider. The dose of Lokelma may need to be adjusted [see Warnings and Precautions (5.3)].

Diagnostic Testing

Advise patients to notify their physician prior to an abdominal X-ray [see Warnings and Precautions (5.4)].

Drug Interactions

Advise patients who are taking other oral medications to separate dosing of LOKELMA by at least 2 hours (before or after) [see Drug Interactions (7)].

Diet

Advise patients to adjust dietary sodium, if appropriate [see Warnings and Precautions (5.2)].

U.S. Patent No: 6332985, 8808750, 8877255, 8802152, 9592253

© AstraZeneca 2024

Manufactured by: AstraZeneca Pharmaceuticals LP, Wilmington, DE 19850

PACKAGE/LABEL PRINCIPAL DISPLAY PANEL – 5 g

NDC 0310-1105-30 Contains 30 packets

LOKELMA®

(sodium zirconium cyclosilicate)

for oral suspension

5 g per packet

Rx Only

AstraZeneca

PACKAGE/LABEL PRINCIPAL DISPLAY PANEL – 10 g

NDC 0310-1110-30 Contains 30 packets

LOKELMA®

(sodium zirconium cyclosilicate)

for oral suspension

10 g per packet

Rx Only

AstraZeneca